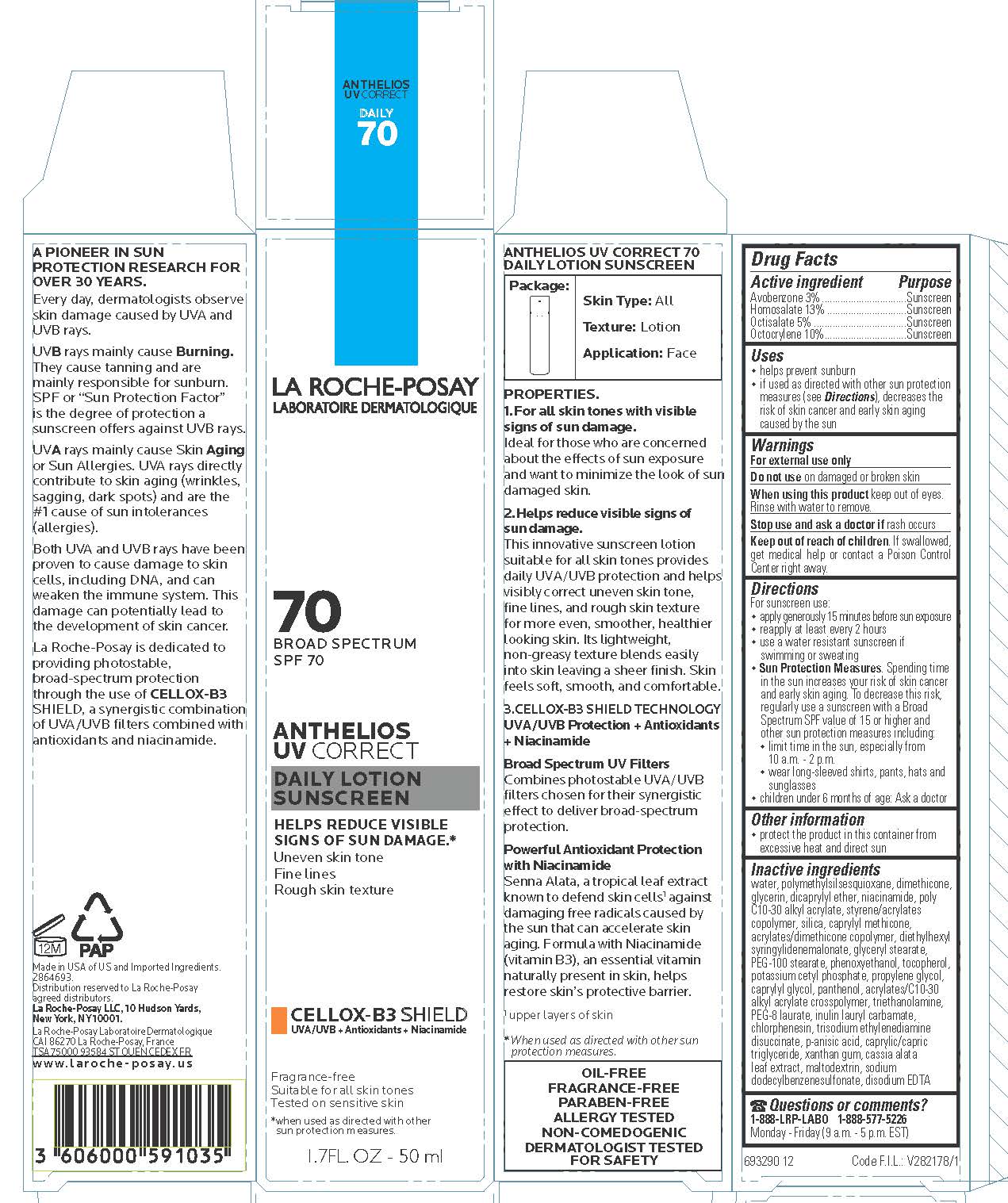 DRUG LABEL: La Roche Posay Laboratoire Dermatologique Anthelios UV Correct Broad Spectrum SPF 70 Daily Sunscreen
NDC: 49967-910 | Form: LOTION
Manufacturer: L'Oreal USA Products Inc
Category: otc | Type: HUMAN OTC DRUG LABEL
Date: 20231231

ACTIVE INGREDIENTS: Avobenzone 30 mg/1 mL; Homosalate 130 mg/1 mL; Octisalate 50 mg/1 mL; Octocrylene 100 mg/1 mL
INACTIVE INGREDIENTS: WATER; POLYMETHYLSILSESQUIOXANE (4.5 MICRONS); DIMETHICONE; GLYCERIN; DICAPRYLYL ETHER; NIACINAMIDE; BEHENYL ACRYLATE POLYMER; STYRENE/ACRYLAMIDE COPOLYMER (500000 MW); SILICON DIOXIDE; CAPRYLYL TRISILOXANE; 2-ETHYLHEXYL ACRYLATE, METHACRYLATE, METHYL METHACRYLATE, OR BUTYL METHACRYLATE/HYDROXYPROPYL DIMETHICONE COPOLYMER (30000-300000 MW); DIETHYLHEXYL SYRINGYLIDENEMALONATE; GLYCERYL MONOSTEARATE; PEG-100 STEARATE; PHENOXYETHANOL; TOCOPHEROL; POTASSIUM CETYL PHOSPHATE; PROPYLENE GLYCOL; CAPRYLYL GLYCOL; PANTHENOL; CARBOMER INTERPOLYMER TYPE A (ALLYL SUCROSE CROSSLINKED); TROLAMINE; PEG-8 LAURATE; CHLORPHENESIN; TRISODIUM ETHYLENEDIAMINE DISUCCINATE; P-ANISIC ACID; MEDIUM-CHAIN TRIGLYCERIDES; XANTHAN GUM; SENNA ALATA LEAF; MALTODEXTRIN; SODIUM DODECYLBENZENESULFONATE; EDETATE DISODIUM ANHYDROUS

Drug Facts

Active ingredients

Avobenzone 3%

Homosalate 13%

Octisalate 5%

Octocrylene 10%

Uses

- helps prevent sunburn
- if used as directed (see Directions), decreases the risk of skin cancer and early skin aging caused by the sun

Warnings

For external use only

Do not use

on damaged or broken skin

When using this product

keep out of eyes. Rinse with water to remove.

Stop use and ask a doctor if

rash occurs

Keep out of reach of children.

If swallowed, get medical help or contact a Poison Control Center right away.

Directions

For sunscreen use:

- apply generously 15 minutes before sun exposure
- reapply at least every 2 hours
- use a water resistant sunscreen if swimming or sweating
- Sun Protection Measures. Spending time in the sun increases your risk of skin cancer and early skin aging. To decrease this risk regularly use a sunscreen with a Broad Spectrum SPF value of 15 of higher and other sun protection measures including:

- limit time in the sun, especially from 10 a.m. - 2 p.m.

- wear long-sleeved shirts, pants, hats and sunglasses

- children under 6 months of age: Ask a doctor

Purpose

Sunscreen

Other information

- protect the product in this container from excessive heat and direct sun

Inactive ingredients

water, polymethylsilsesquioxane, dimethicone, glycerin, dicaprylyl ether, niacinamide, poly c10-30 alkyl acrylate, styrene/acrylates copolymer, silica, caprylyl methicone, acrylates/dimethicone copolymer, diethylhexyl syringylidenemalonate, glyceryl stearate, PEG-100 stearate, phenoxyethanol, tocopherol, potassium cetyl phosphate, propylene glycol, caprylyl glycol, panthenol, acrylates/c10-30 alkyl acrylate crosspolymer, triethanolamine, PEG-8 laurate, inulin lauryl carbamate, chlorphenesin, trisodium ethylenediamine disuccinate, p-anisic acid, caprylic/capric triglyceride, xanthan gum, cassia alata leaf extract, maltodextrin, sodium dodecylbenzenesulfonate, disodium EDTA

Questions or comments?

1-888-LRP-LABO 1-888-577-5226

Monday - Friday (9 a.m. - 5 p.m. EST)